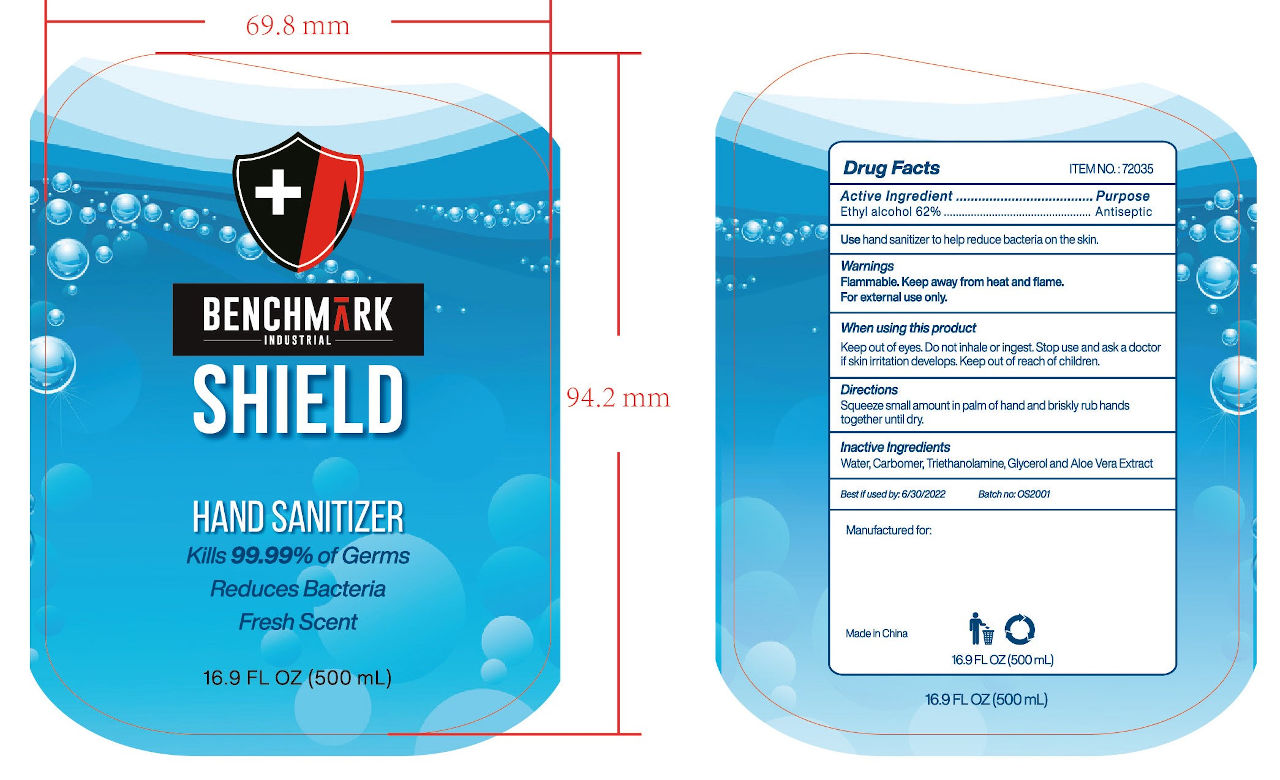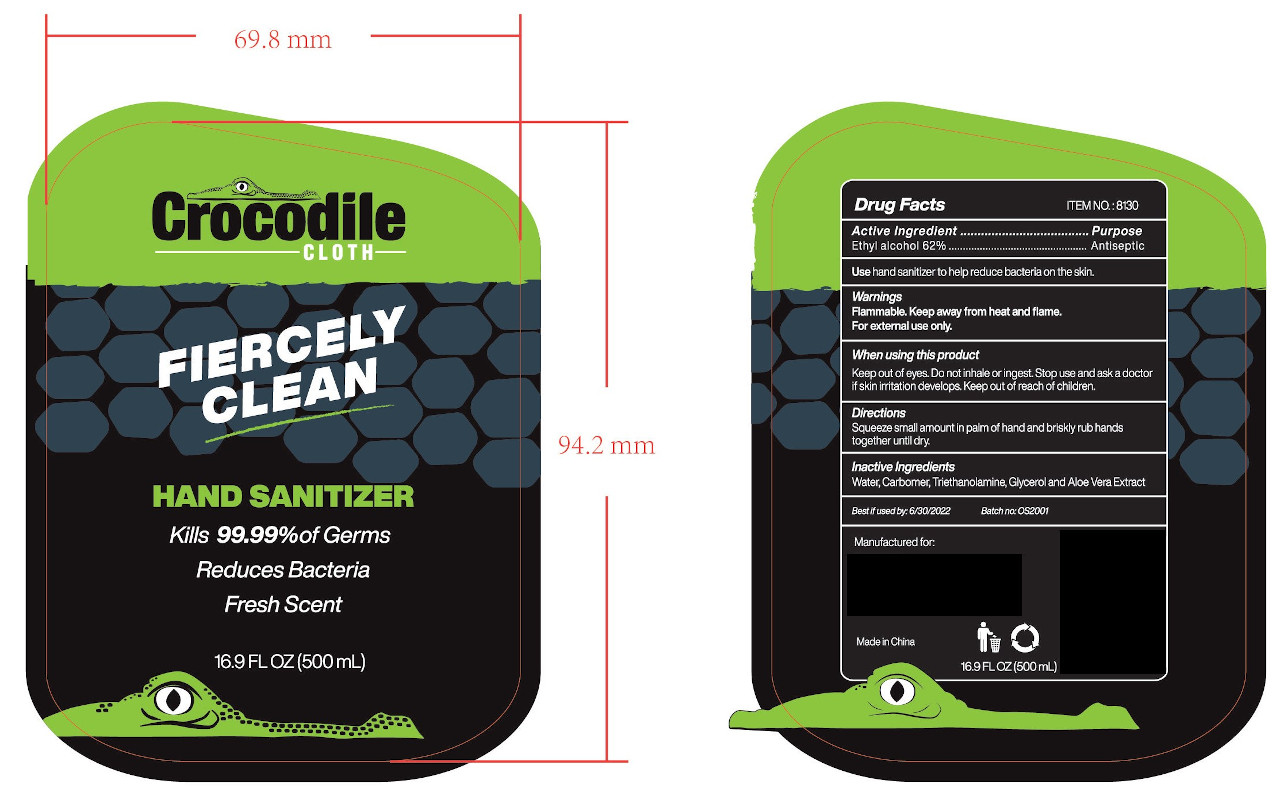 DRUG LABEL: HAND SANITIZER
NDC: 47993-280 | Form: GEL
Manufacturer: NINGBO JIANGBEI OCEAN STAR TRADING CO.,LTD
Category: otc | Type: HUMAN OTC DRUG LABEL
Date: 20201105

ACTIVE INGREDIENTS: ALCOHOL 62 g/112 mL
INACTIVE INGREDIENTS: CARBOMER 940; TRIETHANOLAMINE BENZOATE; ALOE VERA LEAF; WATER; GLYCERIN

47993-280

Active ingredients

Ethyl alcohol 62%

PURPOSE

Antiseptic

Uses：

Hand sanitizer to help reduce bacteria on the skin.

Warnings:

Flammable. keep away from heat and flame. For external use only.

When using this product.

Keep out of eyes. Do not inhale or ingest. Stop use and ask a doctor if skin irritation develops. Keep out of reach of children.

Keep out of reach of children.

Directions:

Squeeze small amount in palm of hand and briskly rub hands together until dry.

Inactive Ingredients:

Water,Carbomer,Triethanolamine,Glycerol and Aloe Vera Extract.